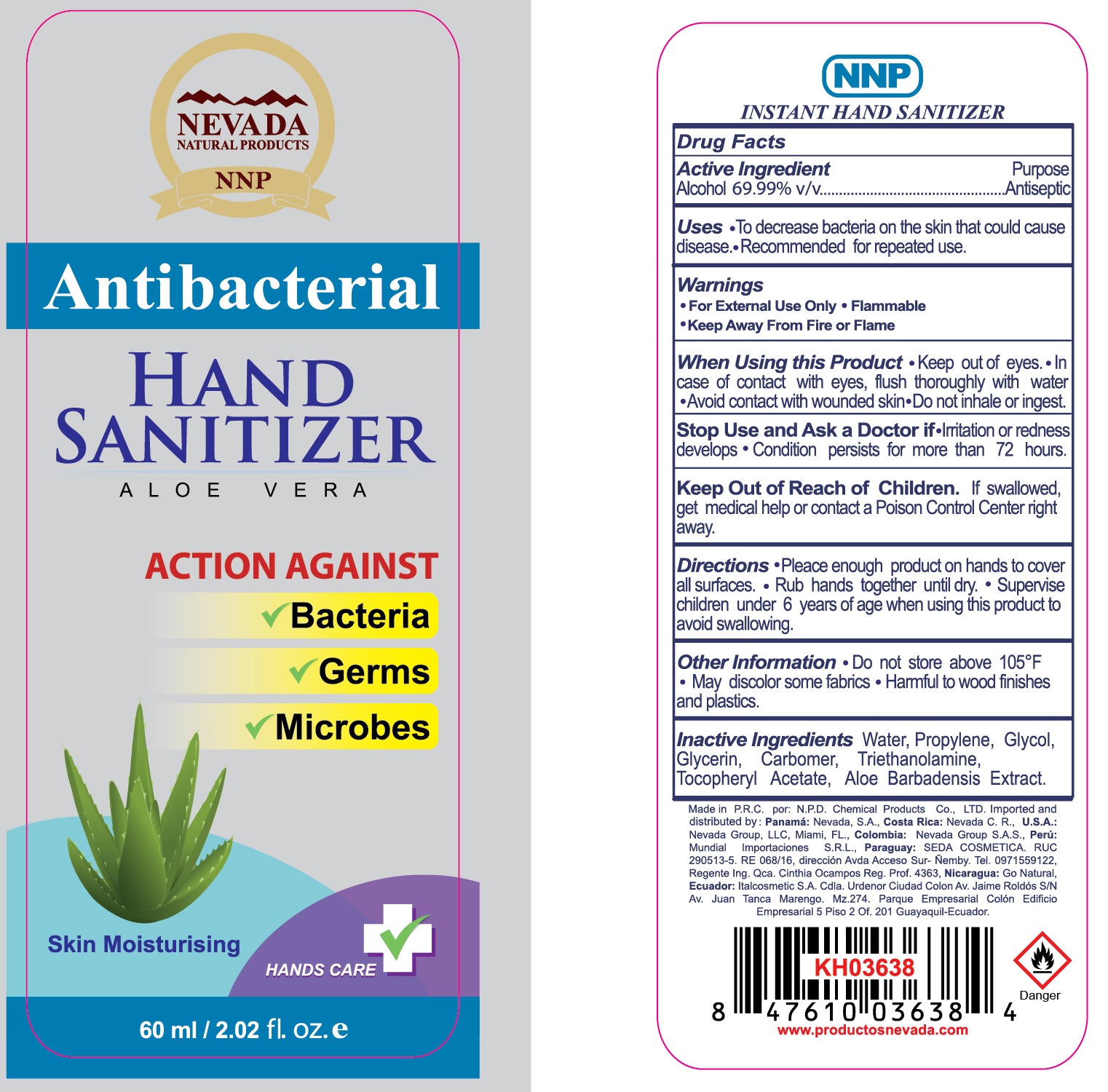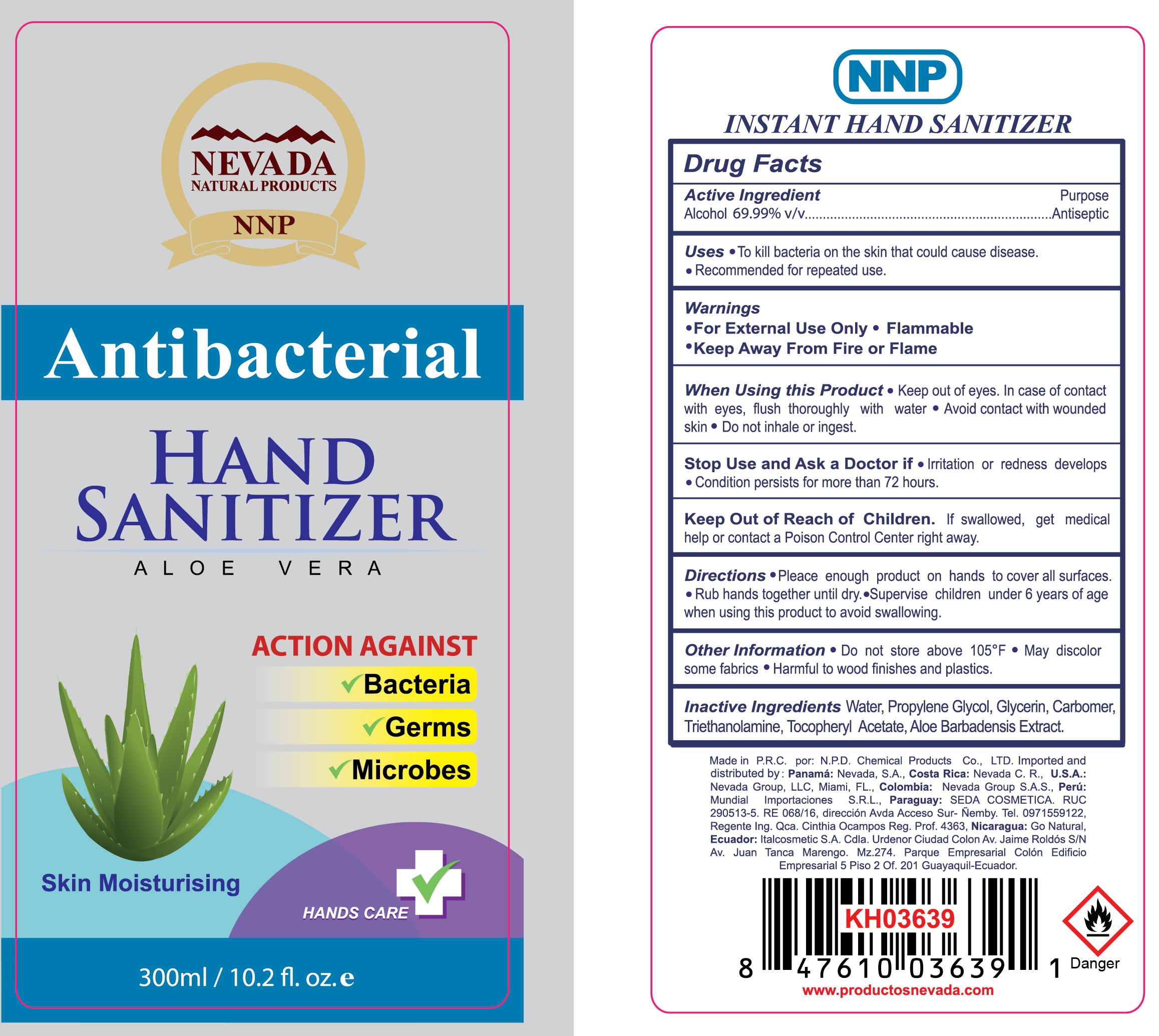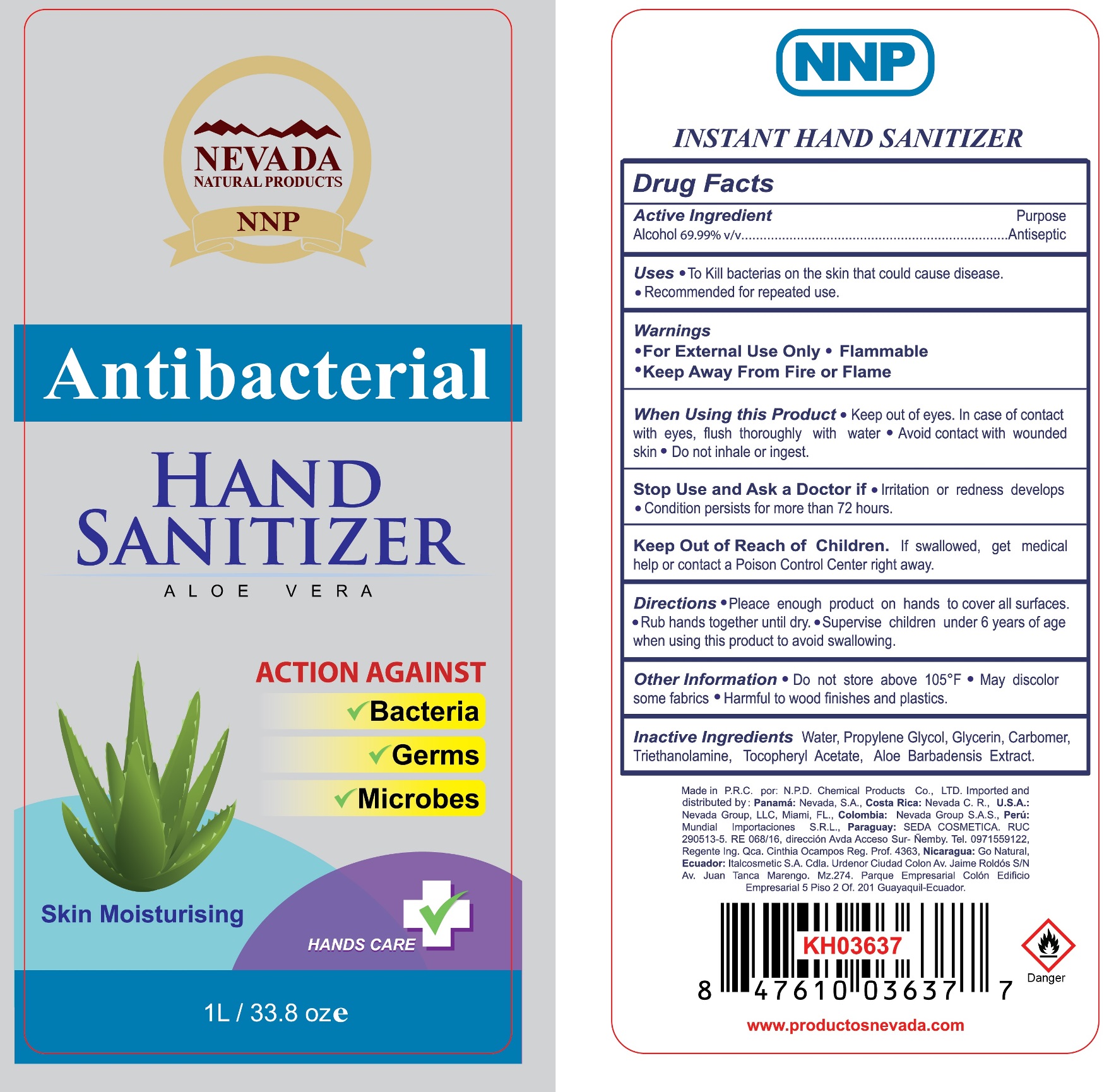 DRUG LABEL: NNP Hand Sanitizer
NDC: 78462-007 | Form: GEL
Manufacturer: Nevada Zona Libre, S.A.
Category: otc | Type: HUMAN OTC DRUG LABEL
Date: 20200603

ACTIVE INGREDIENTS: ALCOHOL 0.6999 mL/1 mL
INACTIVE INGREDIENTS: WATER; PROPYLENE; ETHYLENE GLYCOL; GLYCERIN; CARBOMER HOMOPOLYMER, UNSPECIFIED TYPE; TROLAMINE; .ALPHA.-TOCOPHEROL ACETATE; ALOE VERA LEAF

NNP Hand Sanitizer

Active Ingredient

Alcohol 69.99% v/v

Purpose

Antiseptic

Uses

- To decrease bacteria on the skin that could cause disease.
- Recommended for repeated use.

Warnings

- For External Use Only
- Flammable
- Keep Away From Fire or Flame

When Using this Product

- Keep out of eyes.
- In case of contact with eyes, flush thoroughly with water
- Avoid contact with wounded skin
- Do not inhale or ingest.

Stop Use and Ask a Doctor if

- Irritation or redness develops
- Condition persists for more than 72 hourse.

Keep Out of Reach of Children.

If swallowed, get medical help or contact a Poison Control Center right away

Directions

- Pleace enough product on hands to cover all surfaces.
- Rub hands together until dry.
- Supervise children under 6 years of age when using this product to avoid swallowing.

Other Information

- Do not store above 105°F
- May discolor some fabrics
- Harmful to wood finishes and plastics.

Inactive Ingredients

Water, Propylene, Glycol, Glycerin, Carbomer, Triethanolamine, Tocopheryl Acetate, Aloe Barbadensis Extract.